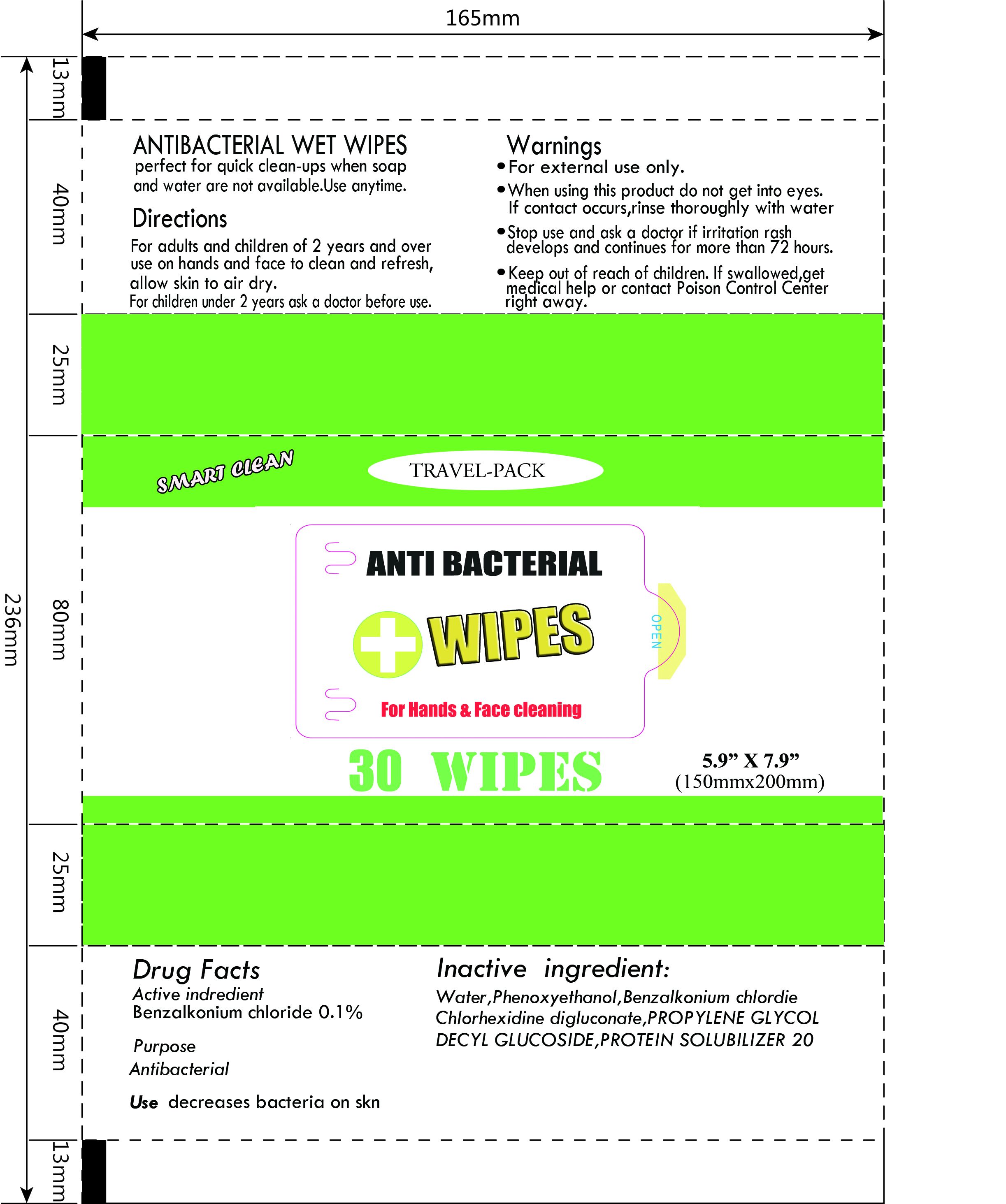 DRUG LABEL: Antibacterial Wet Wipes
NDC: 69304-002 | Form: SWAB
Manufacturer: Lin’an Jiameihui Cleaning Co., Ltd.
Category: otc | Type: HUMAN OTC DRUG LABEL
Date: 20160218

ACTIVE INGREDIENTS: BENZALKONIUM CHLORIDE 0.1 g/100 g
INACTIVE INGREDIENTS: CHLORHEXIDINE; PROPYLENE GLYCOL; PHENOXYETHANOL; POLYSORBATE 20; DECYL GLUCOSIDE; WATER

Active ingredient

Benzalkonium chloride 0.1%

Purpose

Antibacterial

Use

decreases bacteria on skin perfect for quick clean-ups when soap and water are not available.use anytime.

Warnings

For external use only.

When using this product do not get into eyes.

If contact occurs, rinse thoroughly with water.

Stop use and ask a doctor if irritation or rash

develops and continues for more than 72 hours.

Keep out of reach of children. If swallowed, get

medical help or contact aPoisonControlCenter

right away.

Directions

for adults and children of 2 years and over use on hands and face to clean and refresh,allow skin to air dry.

for children under 2 years ask a doctor before use

INACTIVE INGREDIENT

water,Phenoxyethanol,Benzalkonium Chloride,Chlorhexidine digluconate,PROPYLENE GLYCOL,DECYL GLUCOSIDE,PROTEIN SOLUBILIZER 20